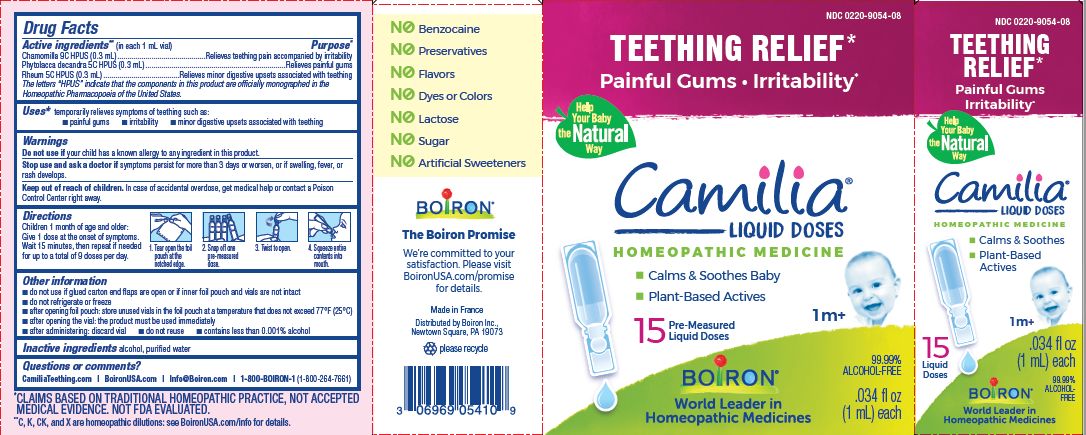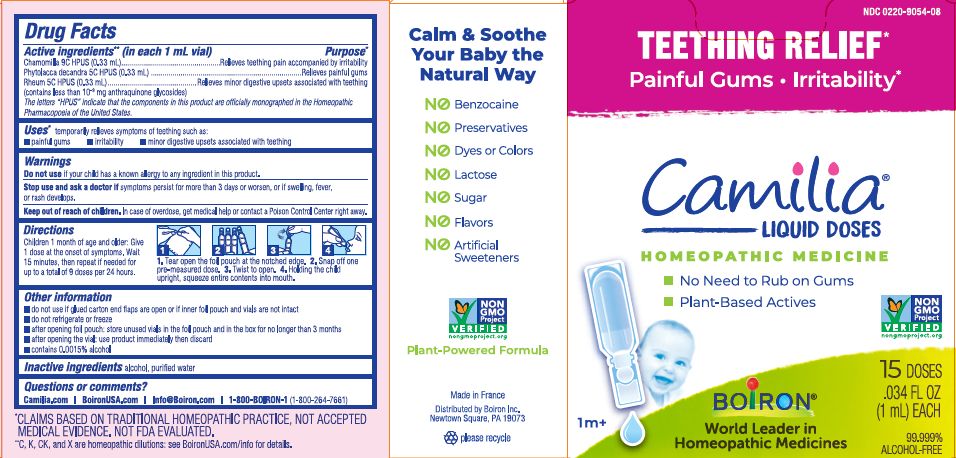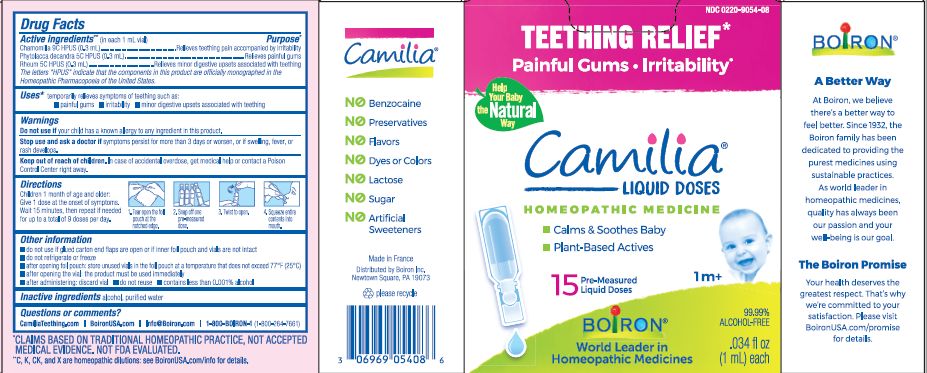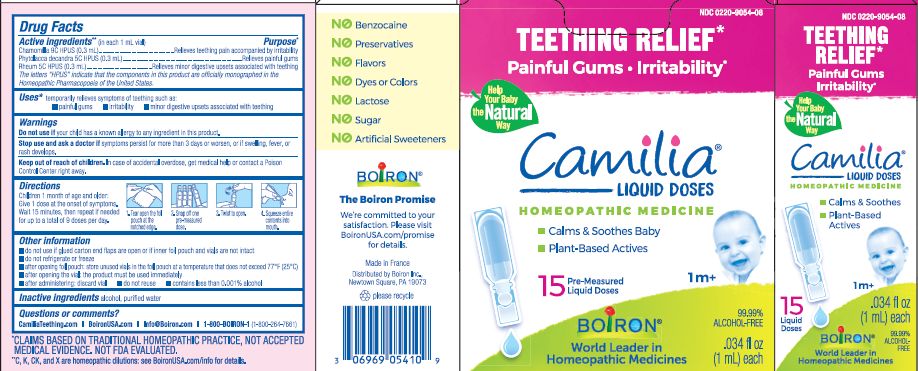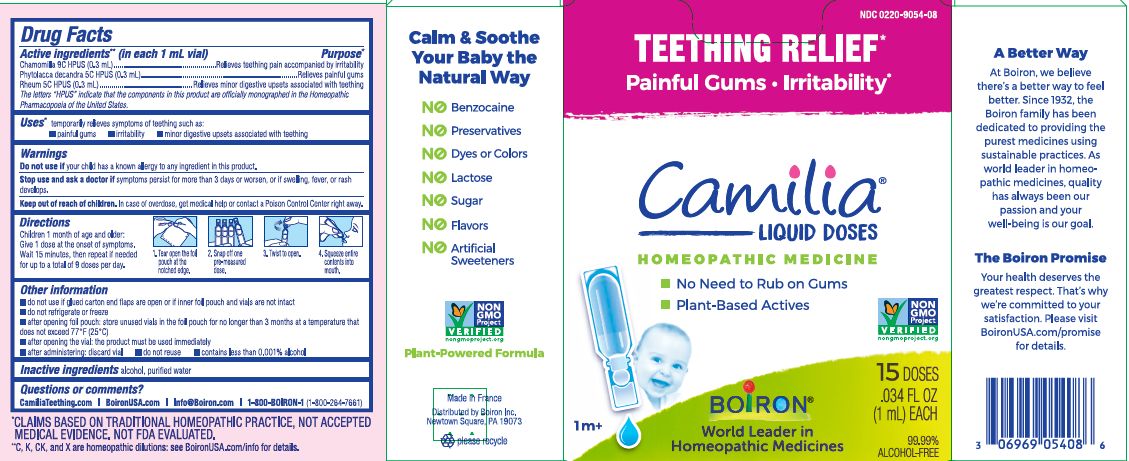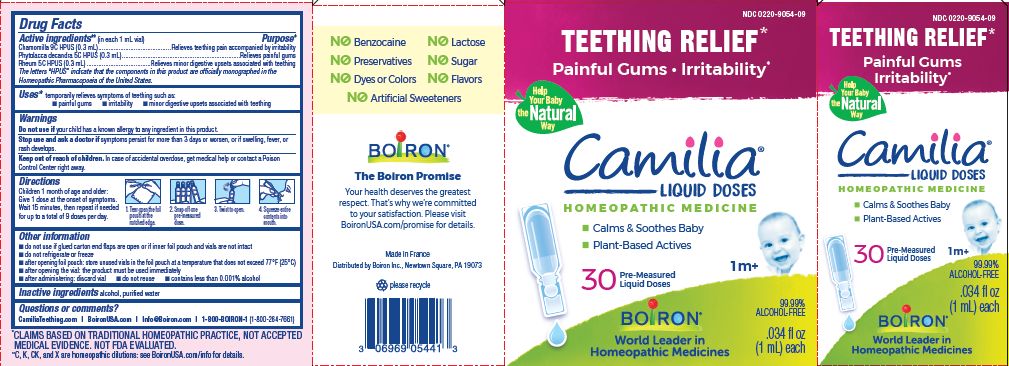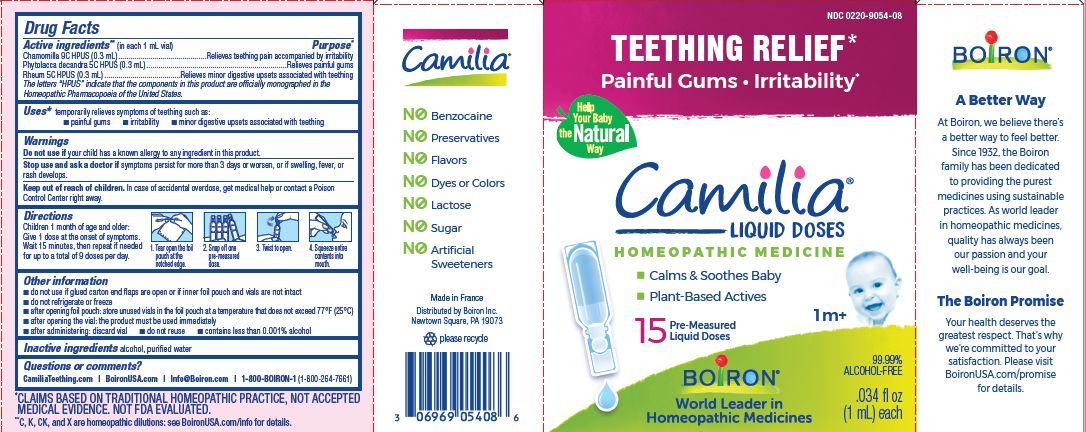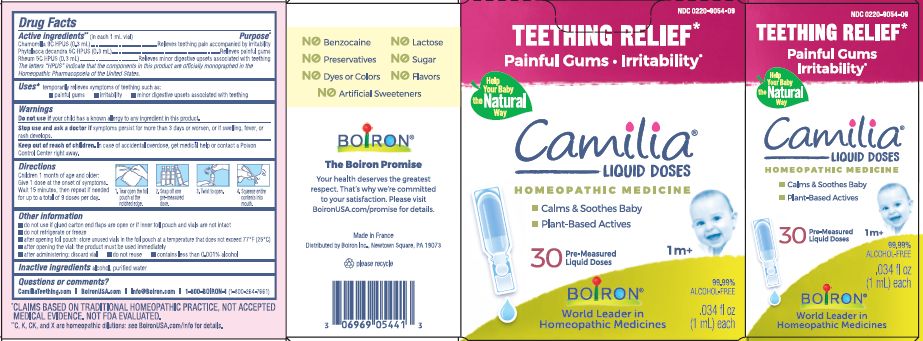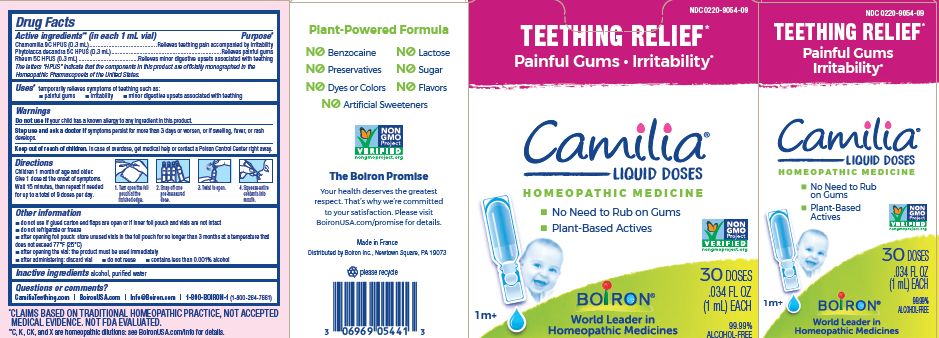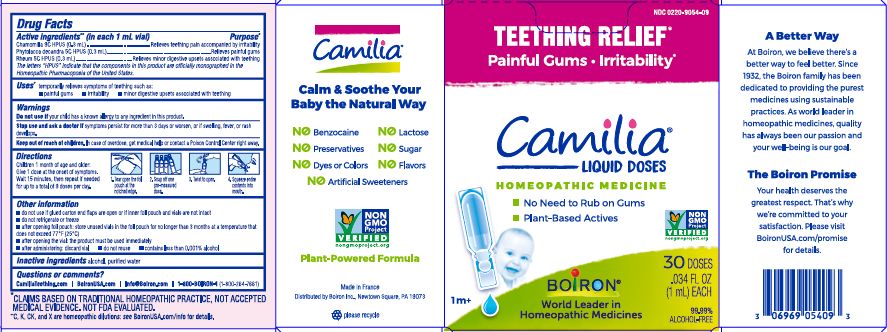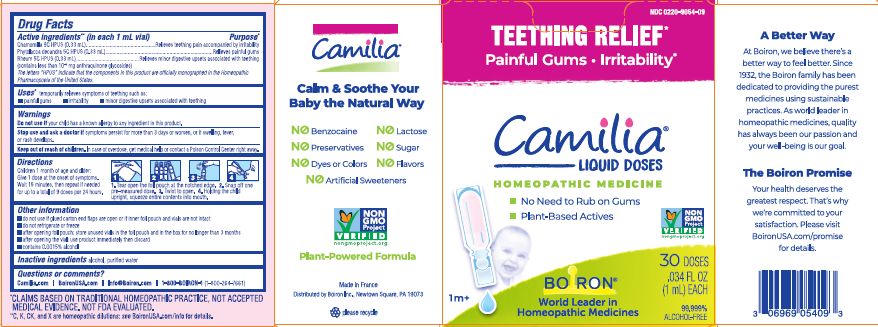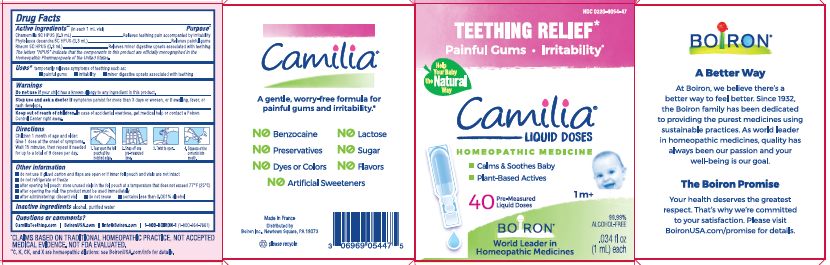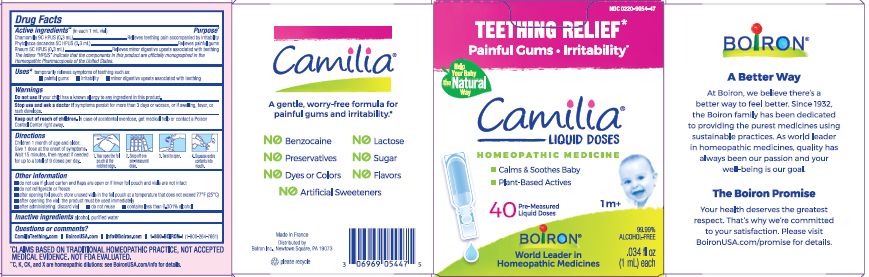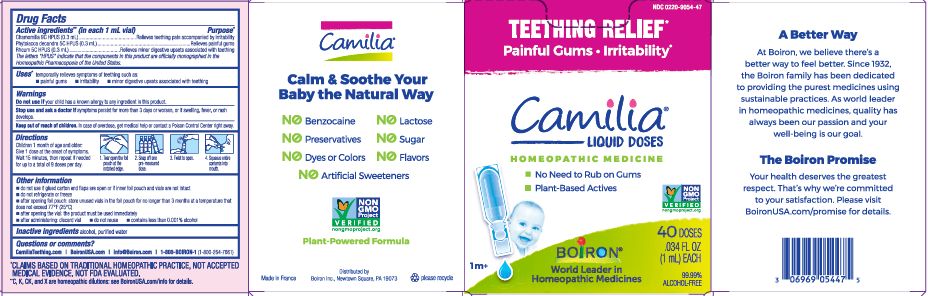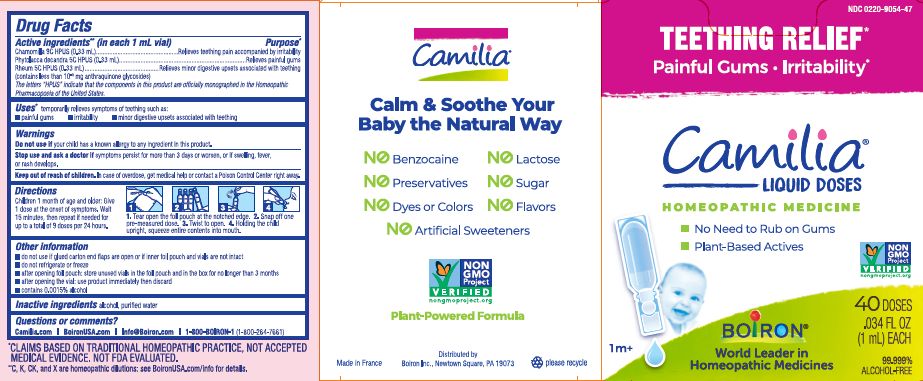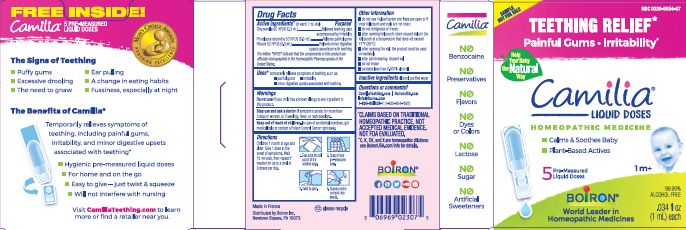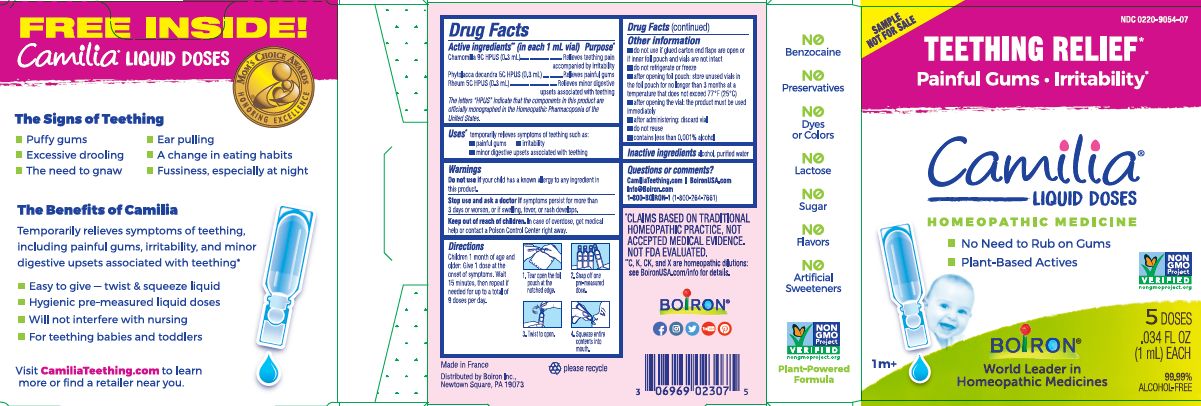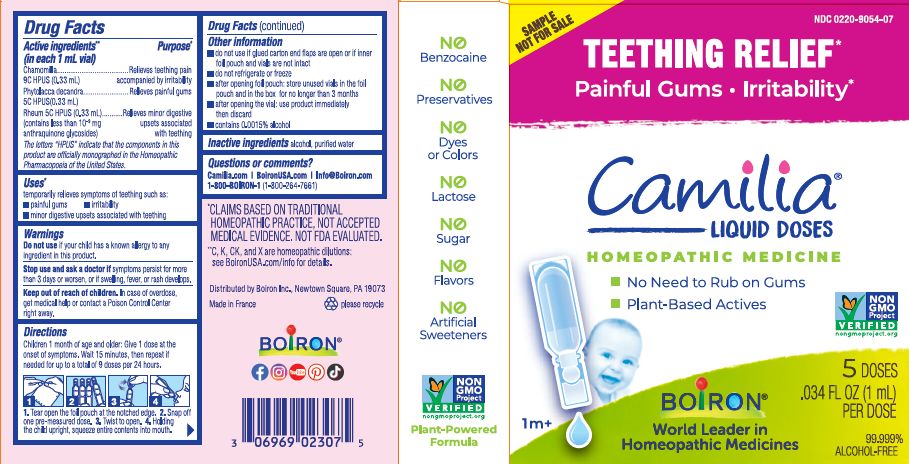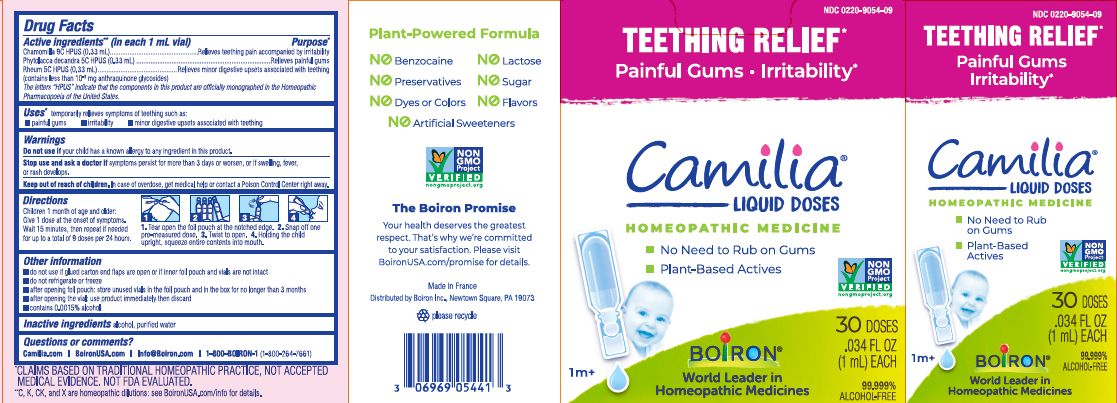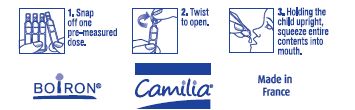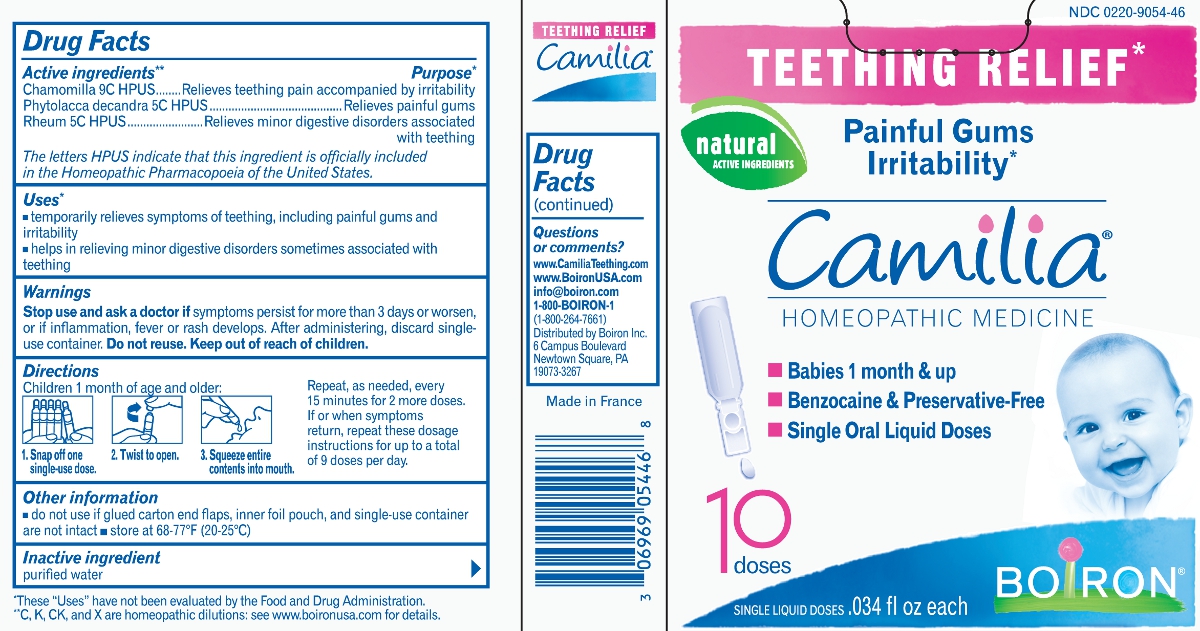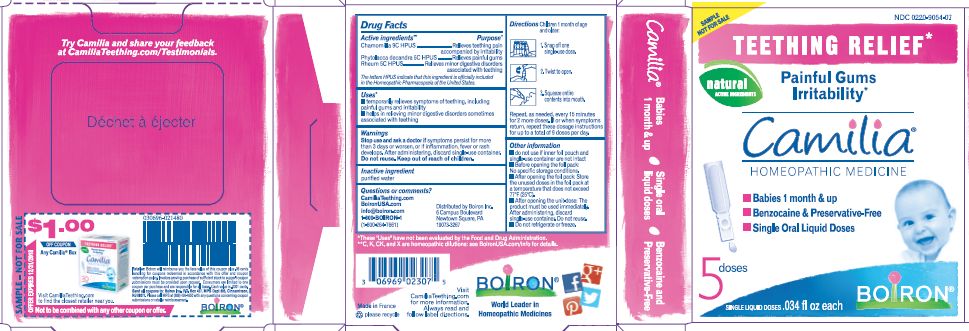 DRUG LABEL: Camilia
NDC: 0220-9054 | Form: LIQUID
Manufacturer: Laboratoires Boiron
Category: homeopathic | Type: HUMAN OTC DRUG LABEL
Date: 20250527

ACTIVE INGREDIENTS: MATRICARIA RECUTITA 9 [hp_C]/1 1; RHUBARB 5 [hp_C]/1 1; PHYTOLACCA AMERICANA ROOT 5 [hp_C]/1 1
INACTIVE INGREDIENTS: WATER; ALCOHOL

Camilia

Active ingredients** (in each 1 mL vial)

Chamomilla 9C HPUS (0.33mL)
Phytolacca decandra 5C HPUS (0.33mL)
Rheum 5C HPUS (0.33mL) (contains less than 10^-9 mg anthraquinone glycosides)

The letters "HPUS" indicate that the components in this product are officially monographed in the Homeopathic Pharmacopoeia of the United States.

Purpose*

Chamomilla 9C HPUS (0.33mL) ... Relieves teething pain accompanied by irritability
Phytolacca decandra 5C HPUS (0.33mL) ... Relieves painful gums
Rheum 5C HPUS (0.333mL) ... Relieves minor digestive upsets associated with teething

Uses*

temporarily relieves symptoms of teething such as:

- painful gums
- irritability
- minor digestive upsets associated with teething

Do not use if your child has a known allergy to any ingredient in this product.

Stop use and ask doctor if symptoms persist for more than 3 days or worsen, or if swelling, fever, or rash develops.

Keep out of reach of children. In case of overdose, get medical help or contact a Poison Control Center right away.

DOSAGE AND ADMINISTRATION

Children 1 month of age and older:

Give 1 dose at the onset of symptoms.

Wait 15 minutes, then repeat if needed for up to a total of 9 doses per 24 hours.
1. Tear open the foil pouch at the notched edge.

2. Snap off one pre-measured dose.

3. Twist to open.

4. Holding the child upright, squeeze entire contents into mouth.

INACTIVE INGREDIENT

alcohol, purified water

do not use if glued carton end flaps are open or if inner foil pouch and vials are not intact

do not refrigerate or freeze

after opening foil pouch: store unused vials in the foil pouch and in the box for no longer than 3 months

after opening the vial: use product immediately then discard

contains less than 0.0015% alcohol

Teething Relief*

Painful Gums Irritability*

*CLAIMS BASED ON TRADITIONAL HOMEOPATHIC PRACTICE, NOT ACCEPTED MEDICAL EVIDENCE. NOT FDA EVALUATED.
**C,K,CK, and X are homeopathic dilutions: see BoironUSA.com/info for details.

HOW SUPPLIED

Single-use liquid doses

.034 fl oz each
(1mL) each

QUESTIONS

Camilia.com

BoironUSA.com

Info@Boiron.com

1-800-BOIRON-1 (1-800-264-7661)

Distributed by Boiron, Inc. Newtown Square, PA 19073

Made in France